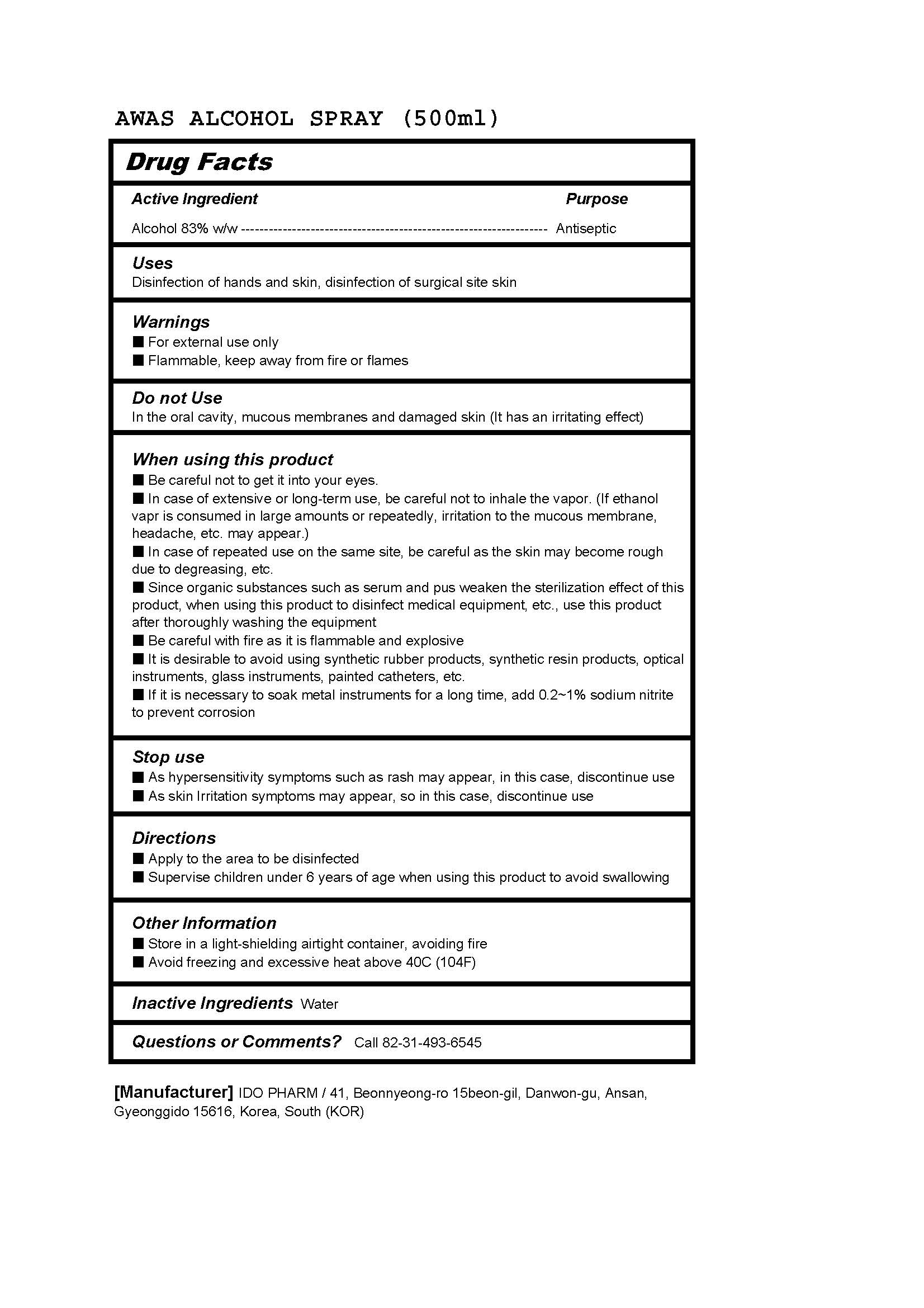 DRUG LABEL: AWAS ALCOHOLSPRAY
NDC: 77039-024 | Form: SPRAY
Manufacturer: IDO PHARM
Category: otc | Type: HUMAN OTC DRUG LABEL
Date: 20250130

ACTIVE INGREDIENTS: ALCOHOL 83 mL/100 mL
INACTIVE INGREDIENTS: WATER

ACTIVE INGREDIENT

alcohol

INACTIVE INGREDIENT

water

PURPOSE

Disinfection of hands and skin, disinfection of surgical site skin

Keep out of reach of children

INDICATIONS AND USAGE

■ Apply to the area to be disinfected
■ Supervise children under 6 years of age when using this product to avoid swallowing

WARNINGS

Flammable, keep away from fire and flames
For external use only

DOSAGE AND ADMINISTRATION

For external use only